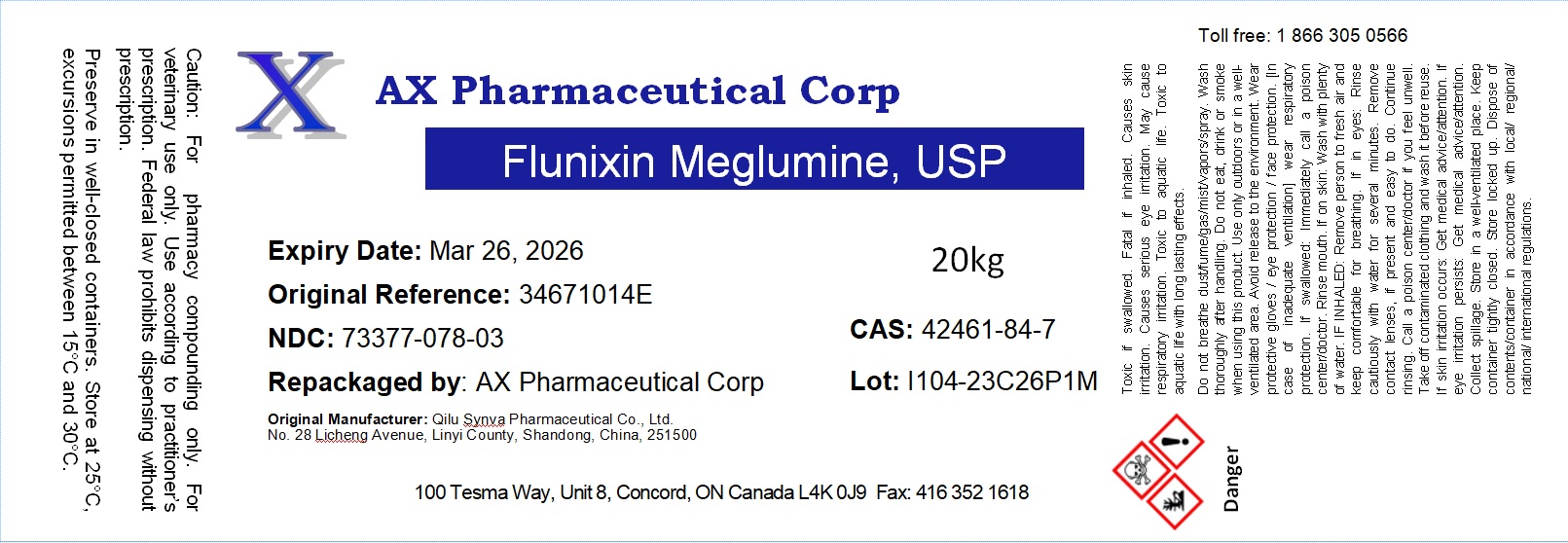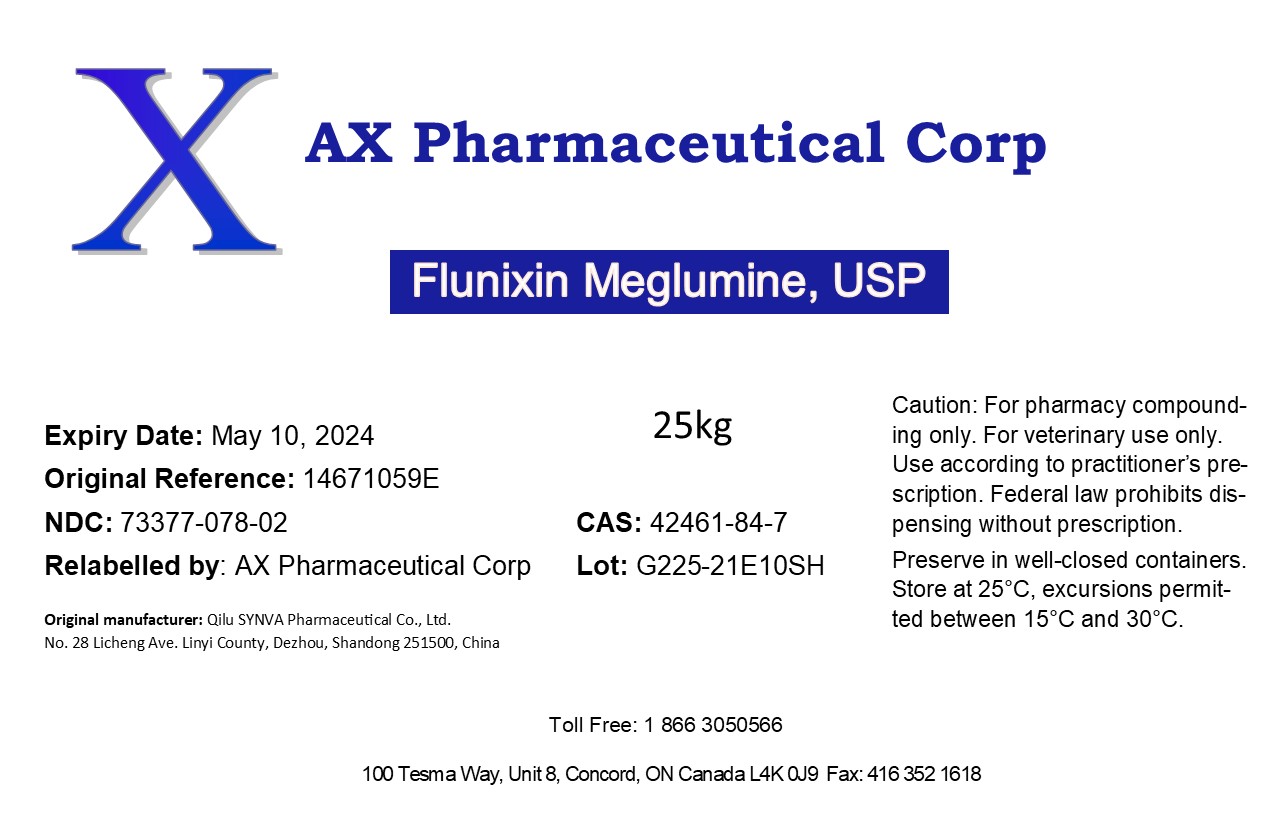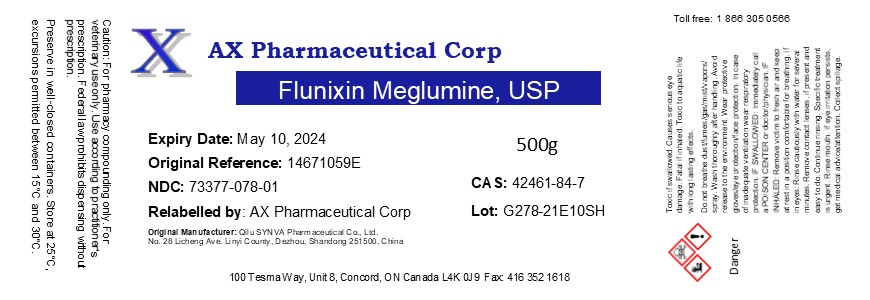 DRUG LABEL: Flunixin Meglumine
NDC: 73377-078 | Form: POWDER
Manufacturer: AX Pharmaceutical Corp
Category: other | Type: BULK INGREDIENT - ANIMAL DRUG
Date: 20231213

ACTIVE INGREDIENTS: FLUNIXIN MEGLUMINE 1 kg/1 kg

Flunixin Meglumine